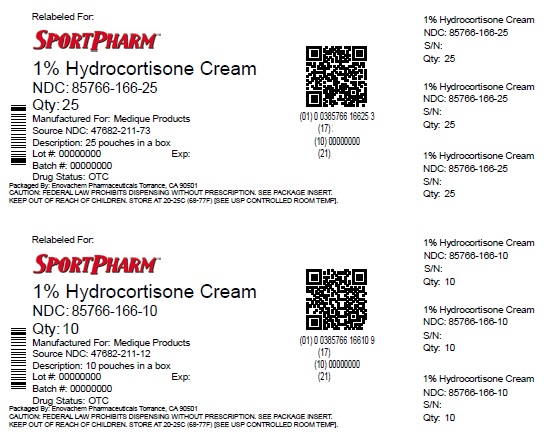 DRUG LABEL: Hydrocortisone
NDC: 85766-166 | Form: CREAM
Manufacturer: Sportpharm LLC
Category: otc | Type: HUMAN OTC DRUG LABEL
Date: 20260223

ACTIVE INGREDIENTS: HYDROCORTISONE 10 mg/1 g
INACTIVE INGREDIENTS: ALCOHOL; METHYLPARABEN; MINERAL OIL; PARAFFIN; PETROLATUM; PROPYLPARABEN; WATER; WHITE WAX

Medi-First 1% hydrocortisone

Drug Facts

Active ingredient

Hydrocortisone 1.0%

Purpose

Anti-itch

Uses

- for the temporary relief of itching associated with minor skin irritations, inflamation and rashes due to eczema, insect bites, poison ivy, poison oak, poison sumac, soaps, detergents, cosmetics, jewelry, seborrheic dermatitis, psoriasis and scrapes
- other uses of this product should be only under the advice and supervision of a doctor

Warnings

For external use only

Do not use

- for the treatment of diaper rash
- with anyother Hydrocortisone product unless you have consulted adoctor
- if you have vaginal discharge, consulkt a doctor

Stop use and ask a doctor if

- condition worsens or lasts more than 7 days, or clears and occurs again within a few days
- you begin use of any other Hydrocortisone product unless you have consulted a doctor
- bleeding occurs

Keep out of reach of children.

If swallowed, get medical help or contact a Poison Control Center right away.

Directions

- for adults and children (2 years of age and older):apply to affected area 3 to 4 times daily
- children under 12 years of age:for external anal itching, consult a doctor
- children under 2 years of age:do not use, consult a doctor
- adults for external anal itching when practical,cleanse the affected area with mild soap and warm water and rinse thoroughly or by patting or blotting with an appropriate cleansing pad
- gently dry by patting or botting with toilet tissue or a soft cloth before application of this product

Other information

- store at room temperature (donot freeze)
- tamper evident, do not use any opened or torn packets

Inactive ingredients

emulsifying wax, ethanol, methylparaben, mineral oil, paraffin, petrolatum, propylparaben, purified water, white wax

Questions or Comments?1-800-634-7680